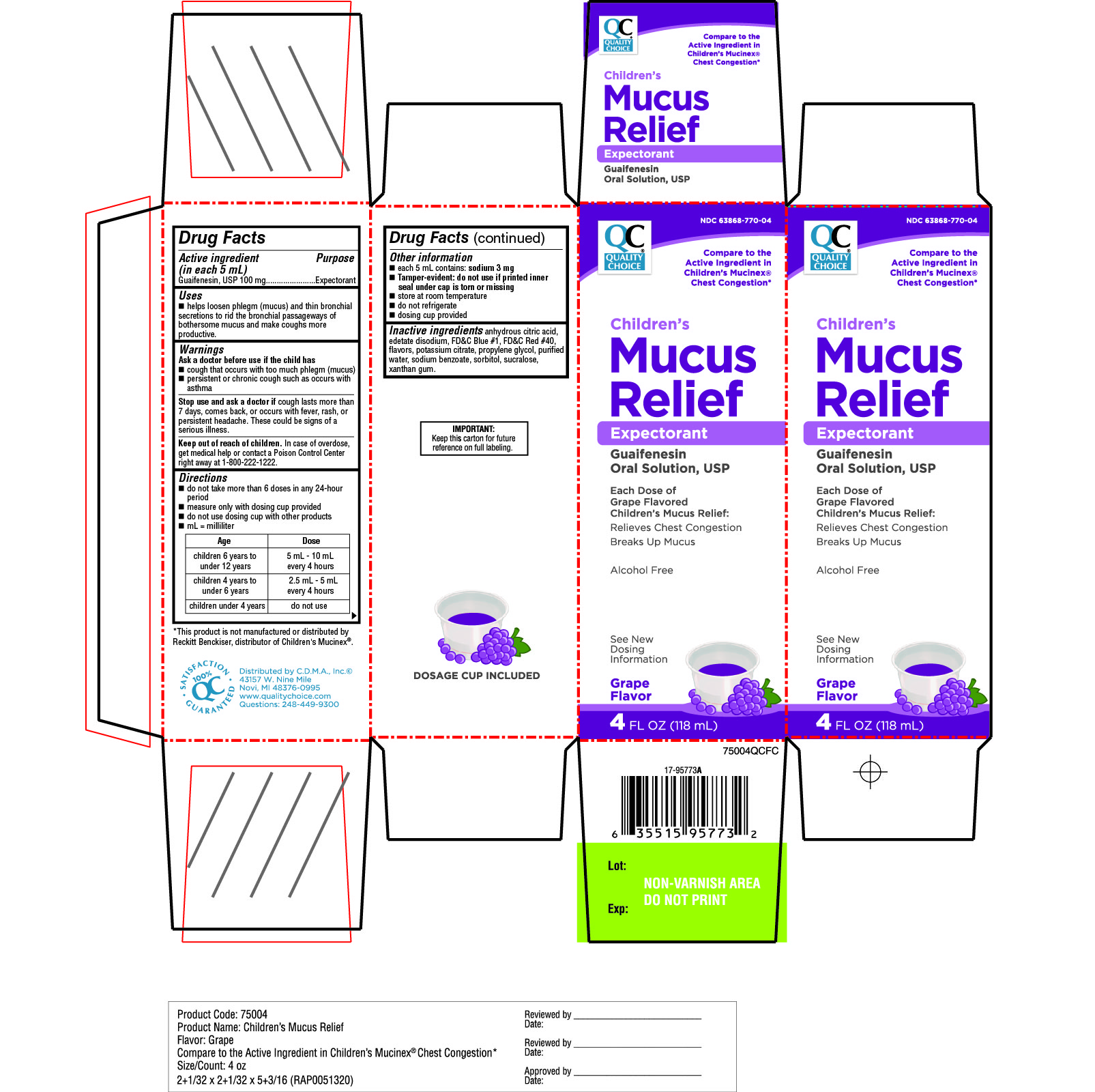 DRUG LABEL: Childrens Mucus Relief

NDC: 63868-770 | Form: SOLUTION
Manufacturer: Chain Drug Manufacturing Assn
Category: otc | Type: HUMAN OTC DRUG LABEL
Date: 20251204

ACTIVE INGREDIENTS: GUAIFENESIN 100 mg/5 mL
INACTIVE INGREDIENTS: ANHYDROUS CITRIC ACID; EDETATE DISODIUM; FD&C BLUE NO. 1; FD&C RED NO. 40; POTASSIUM CITRATE; PROPYLENE GLYCOL; WATER; SODIUM BENZOATE; SORBITOL; SUCRALOSE; XANTHAN GUM

QC Quality Choice Children’s
Mucus Relief Expectorant Grape Flavor 4 FL OZ (118mL)

Drug Facts

Active ingredient (in each 5 mL)

Guaifenesin, USP 100 mg

Purpose

Expectorant

Uses

helps loosen phlegm (mucus) and thin bronchial secretions to rid the bronchial passageways of bothersome mucus and make coughs more productive

Warnings

Ask a doctor before use if the child has

- cough that occurs with too much phlegm (mucus)
- persistent or chronic cough such as occurs with asthma

Stop use and ask a doctor ifcough lasts more than 7 days, comes back, or occurs with fever, rash, or persistent headache. These could be signs of a serious illness.

Keep out of reach of children.In case of overdose, get medical help or contact a Poison Control Center right away.

Directions

- do not take more than 6 doses in any 24-hour period
- measure only with dosing cup provided
- do not use dosing cup with other products
- mL = milliliter

Age | Dose
children 6 years to under 12 years | 5 mL – 10 mL every 4 hours
children 4 years to under 6 years | 2.5 mL – 5 mL every 4 hours
children under 4 years | do not use

Other information

- each 5 mL contains: sodium 3 mg
- Tamper evident: do not use if printed inner seal under cap is torn or missing.
- store at room temperature
- do not refrigerate
- dosing cup provided

Inactive ingredients

anhydrous citric acid, edetate disodium, FD&C Blue #1, FD&C Red #40, flavors, potassium citrate propylene glycol, purified water, sodium benzoate ,sorbitol, sucralose, xanthan gum.

PRINCIPAL DISPLAY PANEL - 118 mL Bottle Carton

QC QUALITY CHOICE NDC 63868-770-04

Children's
Mucus relief

Expectorant

Guaifenesin

Oral Solution, USP

Each Dose of Grape Flavored

Children’s Mucus Relief:

Relieves Chest Congestion

- Breaks up Mucus

Alcohol Free

- See New Dosing Information

Grape
Flavor

4 FL OZ
(118 mL)

IMPORTANT:

Keep this carton for future reference on full labeling.

DOSAGE CUP INCLUDED

*This product is not manufactured or distributed by Reckitt Benckiser, distributor of Children’s Mucinex.®

Distributed by C.D.M.A.,Inc©

43157 W. Nine Mile

Novi, MI 48376-0995

www.qualitychoice.com

Questions: 248-449-9300

QC 100% Satisfaction Guaranteed.